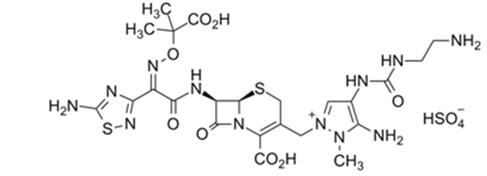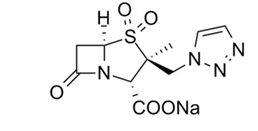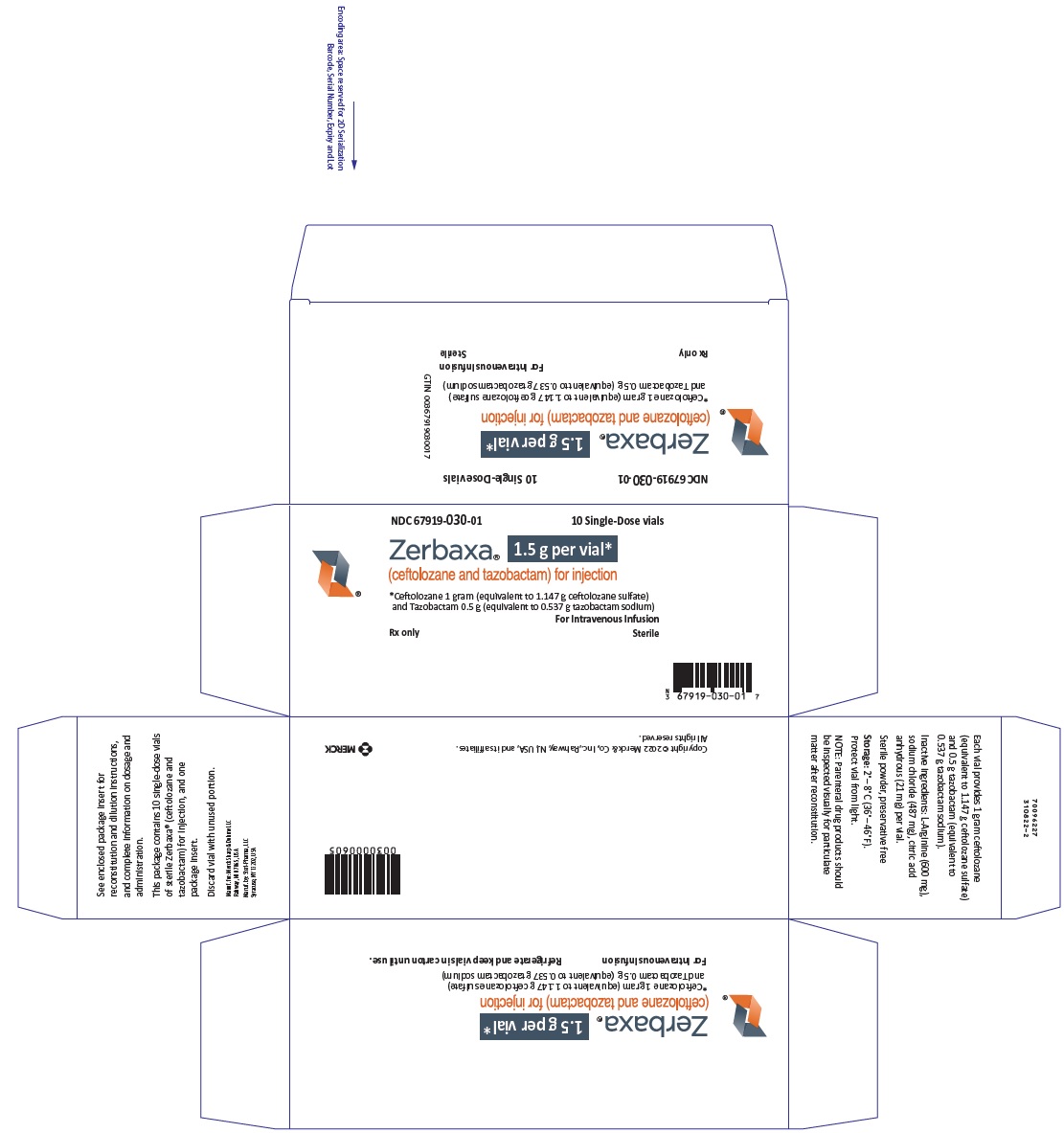 DRUG LABEL: ZERBAXA
NDC: 67919-030 | Form: INJECTION, POWDER, LYOPHILIZED, FOR SOLUTION
Manufacturer: Merck Sharp & Dohme LLC
Category: prescription | Type: HUMAN PRESCRIPTION DRUG LABEL
Date: 20241104

ACTIVE INGREDIENTS: ceftolozane sulfate 1 g/10 mL; tazobactam sodium 0.5 g/10 mL
INACTIVE INGREDIENTS: Arginine 600 mg/10 mL; sodium chloride 487 mg/10 mL; anhydrous citric acid 21 mg/10 mL

HIGHLIGHTS OF PRESCRIBING INFORMATION

These highlights do not include all the information needed to use ZERBAXA safely and effectively. See full prescribing information for ZERBAXA.
ZERBAXA® (ceftolozane and tazobactam) for injection, for intravenous use
Initial U.S. Approval: 2014

RECENT MAJOR CHANGES

Indications and Usage (1) | 4/2022
Dosage and Administration (2) | 4/2022

1 INDICATIONS AND USAGE

ZERBAXA (ceftolozane and tazobactam) is a combination of ceftolozane, a cephalosporin antibacterial, and tazobactam, a beta-lactamase inhibitor, indicated for the treatment of the following infections caused by designated susceptible microorganisms:

- Complicated Intra-abdominal Infections (cIAI), used in combination with metronidazole, in adult and pediatric patients (birth to less than 18 years old). (1.1)
- Complicated Urinary Tract Infections (cUTI), Including Pyelonephritis, in adult and pediatric patients (birth to less than 18 years old). (1.2)
- Hospital-acquired Bacterial Pneumonia and Ventilator-associated Bacterial Pneumonia (HABP/VABP), in adult patients 18 years and older. (1.3)

To reduce the development of drug-resistant bacteria and maintain the effectiveness of ZERBAXA and other antibacterial drugs, ZERBAXA should be used only to treat or prevent infections that are proven or strongly suspected to be caused by bacteria. (1.4)

2 DOSAGE AND ADMINISTRATION

- Administer all doses of ZERBAXA every 8 hours by intravenous infusion over 1 hour in adult and pediatric patients. (2.1, 2.2)
- See Full Prescribing Information for instructions on the preparation of solutions. (2.3)
- For doses above 1.5 g, reconstitute a second vial in the same manner as the first one, withdraw an appropriate volume (per Table 4 in the Full Prescribing Information), and add to the same infusion bag. (2.3)

Recommended Dosage of ZERBAXA by Infection in Adult Patients (18 years or older) with Creatinine Clearance (CrCl) Greater than 50 mL/min (2.1)
Infection | Dose | Duration of Treatment
Complicated Intra-abdominal Infections (cIAI) [Used in conjunction with metronidazole 500 mg intravenously every 8 hours] | 1.5 g | 4 to 14 days
Complicated Urinary Tract Infections (cUTI), Including Pyelonephritis | 1.5 g | 7 days
Hospital-acquired Bacterial Pneumonia and Ventilator-associated Bacterial Pneumonia (HABP/VABP) | 3 g | 8 to 14 days

Recommended Dosage of ZERBAXA by infection in Pediatric Patients (birth to less than 18 years of age) with Estimated Glomerular Filtration Rate (eGFR) [Estimated GFR using an age-appropriate equation for use in the pediatric population] Greater than 50 mL/min/1.73 m^2 (2.2)
Infection | Dose | Duration of Treatment
Complicated Intra-abdominal Infections [Used in conjunction with metronidazole.] | 30 mg/kg up to a maximum dose of 1.5 g [Pediatric patients weighing greater than 50 kg should not exceed a maximum dose of 1.5g] | 5 to 14 days
Complicated Urinary Tract Infections, including Pyelonephritis | 30 mg/kg up to a maximum dose of 1.5 g | 7 to 14 days

Recommended Dosage of ZERBAXA in Adult Patients (18 years or older) with CrCl 50 mL/min or less (2.2)
Estimated CrCl (mL/min) [CrCl estimated using Cockcroft-Gault formula] | cIAI and cUTI, including pyelonephritis | HABP/VABP
30 to 50 | ZERBAXA 750 mg (500 mg and 250 mg) intravenously every 8 hours | ZERBAXA 1.5 g (1 g and 0.5 g) intravenously every 8 hours
15 to 29 | ZERBAXA 375 mg (250 mg and 125 mg) intravenously every 8 hours | ZERBAXA 750 mg (500 mg and 250 mg) intravenously every 8 hours
End-stage renal disease (ESRD) on hemodialysis (HD) | A single loading dose of ZERBAXA 750 mg (500 mg and 250 mg) followed by a ZERBAXA 150 mg (100 mg and 50 mg) maintenance dose administered intravenously every 8 hours for the remainder of the treatment period (on hemodialysis days, administer the dose at the earliest possible time following completion of dialysis) | A single loading dose of ZERBAXA 2.25 g (1.5 g and 0.75 g) followed by a ZERBAXA 450 mg (300 mg and 150 mg) maintenance dose administered intravenously every 8 hours for the remainder of the treatment period (on hemodialysis days, administer the dose at the earliest possible time following completion of dialysis)

3 DOSAGE FORMS AND STRENGTHS

- ZERBAXA 1.5 g (ceftolozane and tazobactam) for injection supplied as a sterile powder for reconstitution in single-dose vials containing ceftolozane 1 g (equivalent to 1.147 g ceftolozane sulfate) and tazobactam 0.5 g (equivalent to 0.537 g tazobactam sodium). (3)

4 CONTRAINDICATIONS

- ZERBAXA is contraindicated in patients with known serious hypersensitivity to the components of ZERBAXA (ceftolozane and tazobactam), piperacillin/tazobactam, or other members of the beta-lactam class. (4)

5 WARNINGS AND PRECAUTIONS

- Decreased efficacy was observed in a Phase 3 cIAI trial in a subgroup of patients with baseline CrCl of 30 to 50 mL/min. Monitor CrCl at least daily in patients with changing renal function and adjust the dose of ZERBAXA accordingly. (5.1)
- Serious hypersensitivity (anaphylactic) reactions have been reported with beta-lactam antibacterial drugs. Exercise caution in patients with known hypersensitivity to beta-lactam antibacterial drugs. If an anaphylactic reaction to ZERBAXA occurs, discontinue the drug and institute appropriate therapy. (5.2)
- Clostridioides difficile-associated diarrhea (CDAD) has been reported with nearly all systemic antibacterial agents, including ZERBAXA. Evaluate if diarrhea occurs. (5.3)

6 ADVERSE REACTIONS

- Adult cIAI, cUTI and HAB/VABP Patients:
  - The most common adverse reactions in adult patients (≥5% in either the cIAI or cUTI indication) are nausea, diarrhea, headache, and pyrexia. (6.1).
  - The most common adverse reactions (≥5% in the HABP/VABP indication) are increase in hepatic transaminases, renal impairment/renal failure, and diarrhea. (6.1)
- Pediatric cIAI and cUTI Patients: The most common adverse reactions in pediatric patients (≥7% in either the cIAI or cUTI indication) are thrombocytosis, diarrhea, pyrexia, leukopenia, abdominal pain, vomiting, increased aspartate aminotransferase, and anemia. (6.1)

To report SUSPECTED ADVERSE REACTIONS, contact Merck Sharp & Dohme LLC at 1-877-888-4231 or FDA at 1-800-FDA-1088 or www.fda.gov/medwatch .

8 USE IN SPECIFIC POPULATIONS

- Pediatrics: Safety and effectiveness in pediatric patients with HABP/VABP have not been established. (8.4)
- Geriatrics: Higher incidence of adverse reactions was observed in patients aged 65 years and older. In a Phase 3 cIAI trial, cure rates were lower in patients 65 years and older. (8.5)

FULL PRESCRIBING INFORMATION

1 INDICATIONS AND USAGE

1.1 Complicated Intra-abdominal Infections

ZERBAXA used in combination with metronidazole is indicated for the treatment of adult and pediatric patients (birth to less than 18 years old) with complicated intra-abdominal infections (cIAI) caused by the following susceptible Gram-negative and Gram-positive microorganisms: Enterobacter cloacae, Escherichia coli, Klebsiella oxytoca, Klebsiella pneumoniae, Proteus mirabilis, Pseudomonas aeruginosa, Bacteroides fragilis, Streptococcus anginosus, Streptococcus constellatus, and Streptococcus salivarius.

1.2 Complicated Urinary Tract Infections, Including Pyelonephritis

ZERBAXA is indicated for the treatment of adult and pediatric patients (birth to less than 18 years old) with complicated urinary tract infections (cUTI), including pyelonephritis, caused by the following susceptible Gram-negative microorganisms: Escherichia coli, Klebsiella pneumoniae, Proteus mirabilis, and Pseudomonas aeruginosa.

1.3 Hospital-acquired Bacterial Pneumonia and Ventilator-associated Bacterial Pneumonia (HABP/VABP)

ZERBAXA is indicated for the treatment of adult patients (18 years and older) with hospital-acquired bacterial pneumonia and ventilator-associated bacterial pneumonia (HABP/VABP), caused by the following susceptible Gram-negative microorganisms: Enterobacter cloacae, Escherichia coli, Haemophilus influenzae, Klebsiella oxytoca, Klebsiella pneumoniae, Proteus mirabilis, Pseudomonas aeruginosa, and Serratia marcescens.

1.4 Usage

To reduce the development of drug-resistant bacteria and maintain the effectiveness of ZERBAXA and other antibacterial drugs, ZERBAXA should be used only to treat or prevent infections that are proven or strongly suspected to be caused by susceptible bacteria. When culture and susceptibility information are available, they should be considered in selecting or modifying antibacterial therapy. In the absence of such data, local epidemiology and susceptibility patterns may contribute to the empiric selection of therapy.

2 DOSAGE AND ADMINISTRATION

2.1 Recommended Dosage in Adult Patients

The recommended dosage of ZERBAXA in adult patients 18 years and older with creatinine clearance (CrCl) greater than 50 mL/min is 1.5 gram (g) (ceftolozane 1 g and tazobactam 0.5 g for cIAI and cUTI and 3 g (ceftolozane 2 g and tazobactam 1 g) for HABP/VABP administered every 8 hours by intravenous infusion over 1 hour The duration of therapy should be guided by the severity and site of infection and the patient’s clinical and bacteriological progress as shown in Table 1.

Table 1: Dosage of ZERBAXA by Infection in Adult Patients (18 years and older) with CrCl [CrCl estimated using Cockcroft-Gault formula] Greater than 50 mL/min
Infection | Dose | Frequency | Infusion Time | Duration of Treatment
Complicated Intra-abdominal Infections [Used in conjunction with metronidazole 500 mg intravenously every 8 hours] | 1.5 g | Every 8 Hours | 1 hour | 4 to 14 days
Complicated Urinary Tract Infections, Including Pyelonephritis | 1.5 g | Every 8 Hours | 1 hour | 7 days
Hospital-acquired Bacterial Pneumonia and Ventilator-associated Bacterial Pneumonia (HABP/VABP) | 3 g | Every 8 Hours | 1 hour | 8 to 14 days

2.2 Recommended Dosage in Pediatric Patients with cIAI or cUTI (birth to less than 18 years of age)

The recommended dosage regimen of ZERBAXA in pediatric patients from birth to less than 18 years of age with cIAI and cUTI with an estimated glomerular filtration rate (eGFR) greater than 50 mL/min/1.73 m^2 is described in Table 2. ZERBAXA is administered every 8 hours by intravenous infusion over 1 hour. The duration of treatment should be guided by the severity and site of infection and the patient’s clinical and bacteriological progress as shown in Table 2. For the treatment of cIAI, metronidazole should be given concurrently.

ZERBAXA is not recommended in pediatric patients who have an eGFR 50 mL/min/1.73m^2 or less [see Use in Specific Populations (8.4)].

There is insufficient information to recommend a dosage regimen for pediatric patients with HABP/VABP [see Use in Specific Populations (8.4)].

Table 2: Dosage of ZERBAXA by infection in Pediatric Patients (birth to less 18 years of age) with eGFR [Estimated GFR using an age-appropriate equation for use in the pediatric population] greater than 50 mL/min/1.73 m^2
Infection | Dose | Frequency | Infusion time | Duration of treatment
Complicated Intra-abdominal Infections [Used in conjunction with metronidazole [see Clinical Studies (14.1)].] | 30 mg/kg up to a maximum dose of 1.5 g [Pediatric patients weighing greater than 50 kg should not exceed a maximum dose of 1.5 g] | Every 8 hours | 1 hour | 5 to 14 days
Complicated Urinary Tract Infections including Pyelonephritis | 30 mg/kg up to a maximum dose of 1.5 g | Every 8 hours | 1 hour | 7 to 14 days

2.3 Dosage Adjustments in Adult Patients with Renal Impairment

Dose adjustment is required for adult patients (18 years and older) with CrCl 50 mL/min or less (Table 3). All doses of ZERBAXA are administered over 1 hour. For patients with changing renal function, monitor CrCl at least daily and adjust the dosage of ZERBAXA accordingly [see Use in Specific Populations (8.6) and Clinical Pharmacology (12.3)].

Table 3: Dosage of ZERBAXA in Adult Patients (18 years and older) with CrCl 50 mL/min or less
Estimated CrCl (mL/min) [CrCl estimated using Cockcroft-Gault formula] | Complicated Intra-abdominal Infections and Complicated Urinary Tract Infections, Including Pyelonephritis | Hospital-acquired Bacterial Pneumonia and Ventilator-associated Bacterial Pneumonia (HABP/VABP)
30 to 50 | 750 mg (500 mg and 250 mg) intravenously every 8 hours | 1.5 g (1 g and 0.5 g) intravenously every 8 hours
15 to 29 | 375 mg (250 mg and 125 mg) intravenously every 8 hours | 750 mg (500 mg and 250 mg) intravenously every 8 hours
End-stage renal disease (ESRD) on hemodialysis (HD) | A single loading dose of 750 mg (500 mg and 250 mg) followed by a 150 mg (100 mg and 50 mg) maintenance dose administered intravenously every 8 hours for the remainder of the treatment period (on hemodialysis days, administer the dose at the earliest possible time following completion of dialysis) | A single loading dose of 2.25 g (1.5 g and 0.75 g) followed by a 450 mg (300 mg and 150 mg) maintenance dose administered intravenously every 8 hours for the remainder of the treatment period (on hemodialysis days, administer the dose at the earliest possible time following completion of dialysis)

2.4 Dosage Adjustments in Pediatric Patients with Renal Impairment

Dosage adjustment of ZERBAXA in pediatric patients (birth to less than 18 years of age) with eGFR 50 mL/min/1.73 m^2 or less has not been determined.

ZERBAXA is not recommended in pediatric patients who have an eGFR 50 mL/min/1.73m^2 or less [see Use in Specific Populations (8.4)].

2.5 Preparation of Solutions

ZERBAXA does not contain a bacteriostatic preservative. Aseptic technique must be followed in preparing the infusion solution.

Preparation of doses:

Constitute each vial of ZERBAXA with 10 mL of sterile water for injection or 0.9% Sodium Chloride for Injection, USP and gently shake to dissolve. The final volume is approximately 11.4 mL per vial. Caution: The constituted solution is not for direct injection.

To prepare the required dose, withdraw the appropriate volume determined from Table 4 from the reconstituted vial(s). Add the withdrawn volume to an infusion bag containing 100 mL of 0.9% Sodium Chloride for Injection, USP or 5% Dextrose Injection, USP. For doses above 1.5 g, reconstitute a second vial in the same manner as the first one, withdraw an appropriate volume (per Table 4), and add to the same infusion bag. Discard unused portion.

Table 4: Preparation of Doses
ZERBAXA (ceftolozane and tazobactam) Dose | Volume to Withdraw from Reconstituted Vial(s)
3 g (2 g and 1 g) | Two vials of 11.4 mL each (entire contents from two vials)
2.25 g (1.5 g and 0.75 g) | 11.4 mL from one vial (entire contents) and 5.7 mL from a second vial
1.5 g (1 g and 0.5 g) | 11.4 mL (entire contents from one vial)
750 mg (500 mg and 250 mg) | 5.7 mL
450 mg (300 mg and 150 mg) | 3.5 mL
375 mg (250 mg and 125 mg) | 2.9 mL
150 mg (100 mg and 50 mg) | 1.2 mL

Inspect drug products visually for particulate matter and discoloration prior to use. ZERBAXA infusions range from clear, colorless solutions to solutions that are clear and slightly yellow. Variations in color within this range do not affect the potency of the product.

2.6 Compatibility

Compatibility of ZERBAXA with other drugs has not been established. ZERBAXA should not be mixed with other drugs or physically added to solutions containing other drugs.

2.7 Storage of Constituted Solutions

Upon constitution with sterile water for injection or 0.9% sodium chloride injection, reconstituted ZERBAXA solution may be held for 1 hour prior to transfer and dilution in a suitable infusion bag.

Following dilution of the solution with 0.9% sodium chloride or 5% dextrose, ZERBAXA is stable for 24 hours when stored at room temperature or 7 days when stored under refrigeration at 2 to 8°C (36 to 46°F). Discard unused portion.

Constituted ZERBAXA solution or diluted ZERBAXA infusion should not be frozen.

3 DOSAGE FORMS AND STRENGTHS

ZERBAXA 1.5 g (ceftolozane and tazobactam) for injection is supplied as a white to yellow sterile powder for reconstitution in single-dose vials; each vial contains ceftolozane 1 g (equivalent to 1.147 g of ceftolozane sulfate) and tazobactam 0.5 g (equivalent to 0.537 g of tazobactam sodium).

4 CONTRAINDICATIONS

ZERBAXA is contraindicated in patients with known serious hypersensitivity to the components of ZERBAXA (ceftolozane and tazobactam), piperacillin/tazobactam, or other members of the beta-lactam class.

5 WARNINGS AND PRECAUTIONS

5.1 Decreased Efficacy in Patients with Baseline Creatinine Clearance of 30 to 50 mL/min

In a subgroup analysis of a Phase 3 cIAI trial of adult patients, clinical cure rates were lower in patients with baseline CrCl of 30 to 50 mL/min compared to those with CrCl greater than 50 mL/min (Table 5). The reduction in clinical cure rates was more marked in the ZERBAXA plus metronidazole arm compared to the meropenem arm. A similar trend was also seen in the cUTI trial. Monitor CrCl at least daily in patients with changing renal function and adjust the dosage of ZERBAXA accordingly [see Dosage and Administration (2.2)].

Table 5: Clinical Cure Rates in a Phase 3 Trial of Adult cIAI Patients by Baseline Renal Function (MITT Population)
Baseline Renal Function | ZERBAXA plus Metronidazole n/N (%) | Meropenem n/N (%)
CrCl greater than 50 mL/min | 312/366 (85.2) | 355/404 (87.9)
CrCl 30 to 50 mL/min | 11/23 (47.8) | 9/13 (69.2)

5.2 Hypersensitivity Reactions

Serious and occasionally fatal hypersensitivity (anaphylactic) reactions have been reported in patients receiving beta-lactam antibacterial drugs.

Before initiating therapy with ZERBAXA, make careful inquiry about previous hypersensitivity reactions to other cephalosporins, penicillins, or other beta-lactams. If this product is to be given to a patient with a cephalosporin, penicillin, or other beta-lactam allergy, exercise caution because cross sensitivity has been established. If an anaphylactic reaction to ZERBAXA occurs, discontinue the drug and institute appropriate therapy.

5.3 Clostridioides difficile-associated Diarrhea

Clostridioides difficile-associated diarrhea (CDAD) has been reported for nearly all systemic antibacterial agents, including ZERBAXA, and may range in severity from mild diarrhea to fatal colitis. Treatment with antibacterial agents alters the normal flora of the colon and may permit overgrowth of C. difficile.

C. difficile produces toxins A and B which contribute to the development of CDAD. CDAD must be considered in all patients who present with diarrhea following antibacterial use. Careful medical history is necessary because CDAD has been reported to occur more than 2 months after the administration of antibacterial agents.

If CDAD is confirmed, discontinue antibacterials not directed against C. difficile, if possible. Manage fluid and electrolyte levels as appropriate, supplement protein intake, monitor antibacterial treatment of C. difficile, and institute surgical evaluation as clinically indicated.

5.4 Development of Drug-resistant Bacteria

Prescribing ZERBAXA in the absence of a proven or strongly suspected bacterial infection or a prophylactic indication is unlikely to provide benefit to the patient and risks the development of drug-resistant bacteria.

6 ADVERSE REACTIONS

The following serious reactions are described in greater detail in the Warnings and Precautions section:

- Hypersensitivity reactions [see Warnings and Precautions (5.2)]
- Clostridioides difficile-associated diarrhea [see Warnings and Precautions (5.3)]

6.1 Clinical Trials Experience

Because clinical trials are conducted under widely varying conditions, adverse reaction rates observed in the clinical trials of a drug cannot be directly compared to rates in the clinical trials of another drug and also may not reflect rates observed in practice.

Adult Patients

Complicated Intra-abdominal Infections and Complicated Urinary Tract Infections, Including Pyelonephritis

ZERBAXA was evaluated in Phase 3 comparator-controlled clinical trials of cIAI and cUTI, which included a total of 1015 patients treated with ZERBAXA (1.5 g every 8 hours, adjusted based on renal function where appropriate) and 1032 patients treated with comparator (levofloxacin 750 mg daily in cUTI or meropenem 1 g every 8 hours in cIAI) for up to 14 days. The mean age of treated patients was 48 to 50 years (range 18 to 92 years), across treatment arms and indications. In both indications, about 25% of the subjects were 65 years of age or older. Most patients (75%) enrolled in the cUTI trial were female, and most patients (58%) enrolled in the cIAI trial were male. Most patients (>70%) in both trials were enrolled in Eastern Europe and were White.

The most common adverse reactions (5% or greater in either indication) occurring in patients receiving ZERBAXA were nausea, diarrhea, headache, and pyrexia. Table 6 lists adverse reactions occurring in 1% or greater of patients receiving ZERBAXA in Phase 3 cIAI and cUTI clinical trials.

Table 6: Adverse Reactions Occurring in 1% or Greater of Adult Patients (18 years and older) Receiving ZERBAXA in Phase 3 cIAI and cUTI Clinical Trials
Adverse Reaction | Complicated Intra-abdominal Infections |  | Complicated Urinary Tract Infections, Including Pyelonephritis
Adverse Reaction | ZERBAXA [The ZERBAXA for injection dose was 1.5 g intravenously every 8 hours, adjusted to match renal function where appropriate. In the cIAI trials, ZERBAXA was given in conjunction with metronidazole.] (N=482) n (%) | Meropenem (N=497) n (%) | ZERBAXA (N=533) n (%) | Levofloxacin (N=535) n (%)
Nausea | 38 (7.9) | 29 (5.8) | 15 (2.8) | 9 (1.7)
Headache | 12 (2.5) | 9 (1.8) | 31 (5.8) | 26 (4.9)
Diarrhea | 30 (6.2) | 25 (5) | 10 (1.9) | 23 (4.3)
Pyrexia | 27 (5.6) | 20 (4) | 9 (1.7) | 5 (0.9)
Constipation | 9 (1.9) | 6 (1.2) | 21 (3.9) | 17 (3.2)
Insomnia | 17 (3.5) | 11 (2.2) | 7 (1.3) | 14 (2.6)
Vomiting | 16 (3.3) | 20 (4) | 6 (1.1) | 6 (1.1)
Hypokalemia | 16 (3.3) | 10 (2) | 4 (0.8) | 2 (0.4)
ALT increased | 7 (1.5) | 5 (1) | 9 (1.7) | 5 (0.9)
AST increased | 5 (1) | 3 (0.6) | 9 (1.7) | 5 (0.9)
Anemia | 7 (1.5) | 5 (1) | 2 (0.4) | 5 (0.9)
Thrombocytosis | 9 (1.9) | 5 (1) | 2 (0.4) | 2 (0.4)
Abdominal pain | 6 (1.2) | 2 (0.4) | 4 (0.8) | 2 (0.4)
Anxiety | 9 (1.9) | 7 (1.4) | 1 (0.2) | 4 (0.7)
Dizziness | 4 (0.8) | 5 (1) | 6 (1.1) | 1 (0.2)
Hypotension | 8 (1.7) | 4 (0.8) | 2 (0.4) | 1 (0.2)
Atrial fibrillation | 6 (1.2) | 3 (0.6) | 1 (0.2) | 0
Rash | 8 (1.7) | 7 (1.4) | 5 (0.9) | 2 (0.4)

Treatment discontinuation due to adverse events occurred in 2.0% (20/1015) of patients receiving ZERBAXA and 1.9% (20/1032) of patients receiving comparator drugs. Renal impairment (including the terms renal impairment, renal failure, and renal failure acute) led to discontinuation of treatment in 5/1015 (0.5%) subjects receiving ZERBAXA and none in the comparator arms.

Increased Mortality

In the cIAI trials (Phase 2 and 3), death occurred in 2.5% (14/564) of patients receiving ZERBAXA and in 1.5% (8/536) of patients receiving meropenem. The causes of death varied and included worsening and/or complications of infection, surgery, and underlying conditions.

Less Common Adverse Reactions in Phase 3 cIAI and cUTI Clinical Trials

The following selected adverse reactions were reported in ZERBAXA-treated subjects at a rate of less than 1%:

Cardiac disorders: tachycardia, angina pectoris
Gastrointestinal disorders: gastritis, abdominal distension, dyspepsia, flatulence, ileus paralytic
General disorders and administration site conditions: infusion site reactions
Infections and infestations: candidiasis including oropharyngeal and vulvovaginal, fungal urinary tract infection
Investigations: increased serum gamma-glutamyl transpeptidase (GGT), increased serum alkaline phosphatase, positive Coombs’ test
Metabolism and nutrition disorders: hyperglycemia, hypomagnesemia, hypophosphatemia
Nervous system disorders: ischemic stroke
Renal and urinary system: renal impairment, renal failure
Respiratory, thoracic, and mediastinal disorders: dyspnea
Skin and subcutaneous tissue disorders: urticaria
Vascular disorders: venous thrombosis

Hospital-acquired Bacterial Pneumonia and Ventilator-associated Bacterial Pneumonia (HABP/VABP)

ZERBAXA was evaluated in a Phase 3 comparator-controlled clinical trial for HABP/VABP, which included a total of 361 patients treated with ZERBAXA (3 g every 8 hours, adjusted based on renal function where appropriate) and 359 patients treated with comparator (meropenem 1 g every 8 hours) for up to 14 days. The mean age of treated patients was 60 years (range 18 to 98 years), across treatment arms. About 44% of the subjects were 65 years of age or older. Most patients (71%) enrolled in the trial were male. All subjects were mechanically ventilated at randomization and 92% were in an intensive care unit (ICU) at randomization. The median APACHE II score was 17, and 33% of subjects had a baseline APACHE II score of ≥20, indicating a high severity of illness for many patients enrolled in this trial.

Table 7 lists adverse reactions occurring in 2% or greater of patients receiving ZERBAXA in a Phase 3 HABP/VABP clinical trial.

Table 7: Adverse Reactions Occurring in 2% or Greater of Adult Patients (18 years and older) Receiving ZERBAXA in a Phase 3 HABP/VABP Clinical Trial
Adverse Reactions | ZERBAXA [The ZERBAXA for injection dose was 3 g intravenously every 8 hours, adjusted to match renal function where appropriate.] N=361 n (%) | Meropenem N=359 n (%)
Hepatic transaminase increased [Includes alanine aminotransferase (ALT) increased, aspartate aminotransferase (AST) increased, hepatic enzyme increased, hypertransaminasemia, liver function test abnormal.] | 43 (11.9) | 26 (7.2)
Renal impairment/renal failure [Includes acute renal failure, anuria, azotemia, oliguria, prerenal failure, renal failure, renal impairment.] | 32 (8.9) | 22 (6.1)
Diarrhea | 23 (6.4) | 25 (7.0)
Intracranial hemorrhage [Includes cerebellar hemorrhage, cerebral hematoma, cerebral hemorrhage, hemorrhage intracranial, hemorrhagic stroke, hemorrhagic transformation stroke, intraventricular hemorrhage, subarachnoid hemorrhage, subdural hematoma.] | 16 (4.4) | 5 (1.4)
Vomiting | 12 (3.3) | 10 (2.8)
Clostridioides difficile colitis [Includes Clostridioides difficile colitis, Clostridioides difficile infection, Clostridioides test positive.] | 10 (2.8) | 2 (0.6)

Treatment discontinuation due to adverse reactions occurred in 1.1% (4/361) of patients receiving ZERBAXA and 1.4% (5/359) of patients receiving meropenem.

Less Common Adverse Reactions in a Phase 3 HABP/VABP Clinical Trial

The following selected adverse reactions were reported in ZERBAXA-treated subjects at a rate of less than 2%:

Investigations: blood alkaline phosphatase increased, gamma-glutamyltransferase increased, Coombs direct test positive

Pediatric Patients

Complicated Intra-abdominal Infections and Complicated Urinary Tract Infections, Including Pyelonephritis

ZERBAXA was evaluated in two blinded, randomized, active-controlled clinical studies in pediatric patients from birth to less than 18 years of age, one in cIAI and the other in cUTI, which included a total of 170 pediatric patients treated with ZERBAXA and 54 pediatric patients treated with the comparator. The ZERBAXA dosing regimen was the same in each trial [see Dosage and Administration (2.2)]. Patients were randomized 3:1 to receive ZERBAXA plus metronidazole or meropenem plus placebo in the cIAI study and ZERBAXA or meropenem in the cUTI study [see Clinical Studies [(14.1, 14.2)]. In these pediatric patients, the type of adverse reactions were generally comparable to those observed in adults. Table 8 lists adverse reactions occurring in 4% or greater of pediatric patients receiving ZERBAXA in either the pediatric cIAI or cUTI clinical trial.

Table 8: Adverse Reactions Occurring in 4% or Greater of Pediatric Patients (birth to less than 18 years of age) Receiving ZERBAXA in either the cIAI or cUTI Clinical Trial
Adverse Reaction | Complicated Intra-abdominal Infections |  | Complicated Urinary Tract Infections, Including Pyelonephritis
Adverse Reaction | ZERBAXA [In the cIAI trials, ZERBAXA was given in conjunction with metronidazole.] (N=70) n (%) | Meropenem (N=21) n (%) | ZERBAXA (N=100) n (%) | Meropenem (N=33) n (%)
Thrombocytosis [Includes platelet count increased.] | 11 (16) | 3 (14) | 9 (9) | 3 (9)
Diarrhea | 12 (17) | 5 (24) | 7 (7) | 3 (9)
Pyrexia [Includes hyperthermia.] | 9 (13) | 3 (14) | 7 (7) | 1 (3)
Leukopenia [Includes neutropenia and neutrophil count decreased.] | 3 (4) | 0 (0) | 8 (8) | 0 (0)
Abdominal pain [Includes upper abdominal pain.] | 8 (11) | 0 (0) | 2 (2) | 1 (3)
AST increased | 5 (7) | 1 (5) | 4 (4) | 2 (6)
Vomiting | 7 (10) | 1 (5) | 1 (1) | 1 (3)
ALT increased | 4 (6) | 1 (5) | 4 (4) | 2 (6)
Anemia | 5 (7) | 0 (0) | 2 (2) | 0 (0)
Phlebitis [Includes superficial phlebitis.] | 4 (6) | 0 (0) | 1 (1) | 1 (3)
Hypertension | 3(4) | 0 (0) | 0 (0) | 1 (3)
Gastritis | 3 (4) | 0 (0) | 0 (0) | 0 (0)
Hypokalemia [Includes blood potassium decreased.] | 3 (4) | 0 (0) | 0 (0) | 0 (0)
Bradypnea [Includes respiratory rate decreased.] | 3 (4) | 0 (0) | 0 (0) | 0 (0)

Laboratory Values

The development of a positive direct Coombs test may occur during treatment with ZERBAXA. The incidence of seroconversion to a positive direct Coombs test was 0.2% in patients receiving ZERBAXA and 0% in patients receiving the comparator in the adult cUTI and cIAI clinical trials. The incidence of seroconversion to a positive direct Coombs test was 31.2% in patients receiving ZERBAXA and 3.6% in patients receiving meropenem in the adult HABP/VABP clinical trial. The incidence of seroconversion to a positive direct Coombs test was 45.3% in patients receiving ZERBAXA and 33.3% in patients receiving meropenem in the pediatric cIAI clinical trial. The incidence of seroconversion to a positive direct Coombs test was 29.7% in patients receiving ZERBAXA and 8.7% in patients receiving meropenem in the pediatric cUTI clinical trial. In clinical trials, there was no evidence of hemolysis in patients who developed a positive direct Coombs test in any treatment group.

8 USE IN SPECIFIC POPULATIONS

8.1 Pregnancy

Risk Summary

There are no data available on ZERBAXA, ceftolozane or tazobactam use in pregnant women to allow assessment of a drug-associated risk of major birth defects, miscarriage or adverse maternal or fetal outcomes. Available data from published prospective cohort studies, case series, and case reports over several decades have not identified an association of cephalosporin use during pregnancy with major birth defects, miscarriage, or other adverse maternal or fetal outcomes (see Data). Neither ceftolozane nor tazobactam produced embryo-fetal toxicity when administered to rodents during the period of organogenesis at ceftolozane doses approximately 3.5 times higher in mice and 2 times higher in rats than the maximum recommended human dose (MRHD) of 2 grams every 8 hours based on plasma AUC comparison or at tazobactam doses approximately 10 times higher in rats than the MRHD of 1 gram every 8 hours based on body surface area comparison. In pre-postnatal studies, where pregnant rats were administered intravenous ceftolozane or intraperitoneal tazobactam in gestation and through the lactation period, ceftolozane was associated with a decrease in auditory startle response in first generation offspring at a dose lower than the MRHD based on AUC comparison, and tazobactam was associated with reduced maternal body weight gain and increased stillbirths at a dose equivalent to approximately 4 times the MRHD and reduced fetal body weights in first generation offspring at a dose approximately equivalent to the MRHD based on body surface area comparison (see Data).

The estimated background risk of major birth defects and miscarriage for the indicated population is unknown. All pregnancies have a background risk of birth defect, loss, or other adverse outcomes. In the U.S. general population, the estimated background risk of major birth defects and miscarriage in clinically recognized pregnancies is 2 to 4% and 15 to 20%, respectively.

Data

Human Data

While available studies with multiple cephalosporins cannot definitively establish the absence of risk, published data from prospective cohort studies, case series, and case reports over several decades have not identified an association of cephalosporin use during pregnancy with major birth defects, miscarriage, or other adverse maternal or fetal outcomes. Available studies have methodologic limitations, including small sample size, retrospective data collection, and inconsistent comparator groups.

Animal Data

Ceftolozane

Embryo-fetal development studies were performed in mice administered intravenous ceftolozane at doses of 300, 1000, and 2000 mg/kg/day during the period of organogenesis (Gestation Day 6 through 15) and in rats administered intravenous ceftolozane in doses of 100, 300, and 1000 mg/kg/day during the period of organogenesis (Gestation Day 6 through 17). In mice, ceftolozane was not associated with maternal or embryo-fetal toxicity with doses up to the highest dose of 2000 mg/kg/ day (approximately 3.5 times the MRHD of 2 grams every 8 hours based on plasma AUC comparison). In rats, no embryo-fetal toxicity was observed, but maternal body weight gain was reduced at a ceftolozane dose of 1000 mg/kg/day. No adverse maternal effects in rats were observed at a dose of 300 mg/kg/day and no adverse embryo-fetal effects were observed at a dose of 1000 mg/kg/day (respectively equivalent to approximately 0.7- and 2-times the MRHD based on plasma AUC comparison).

In a pre-postnatal study in rats, intravenous ceftolozane administered during pregnancy and lactation (Gestation Day 6 through Lactation Day 20) was associated with a decrease in auditory startle response in postnatal Day 60 male pups at maternal doses greater than or equal to 300 mg/kg/day. No adverse effects were observed in rats at a dose of 100 mg/kg/day, a dose lower than the MRHD of 2 grams every 8 hours based on plasma AUC comparison.

Tazobactam

In an embryo-fetal study in rats, tazobactam was administered intravenously during the period of organogenesis (Gestation Day 7 through 17) at doses of 125, 500, and 3000 mg/kg/day. The high dose of 3000 mg/kg/day produced maternal toxicity (decreased food consumption and body weight gain) but was not associated with fetal toxicity. No adverse maternal effects were observed at a dose of 500 mg/kg/day and no adverse fetal effects were observed at a dose of 3000 mg/kg/day (respectively equivalent to approximately 2- and 10-times the MRHD of 1 gram every 8 hours based on body surface area comparison). In rats, tazobactam was shown to cross the placenta. Concentrations in the fetus were less than or equal to 10% of those found in maternal plasma.

In a pre-postnatal study in rats, tazobactam administered intraperitoneally in doses of 40, 320, and 1280 mg/kg/day at the end of gestation and during lactation (Gestation Day 17 through Lactation Day 21) was associated with decreased maternal food consumption and body weight gain at the end of gestation and significantly more stillbirths at the high dose of 1280 mg/kg/day. No effects on the physical development, neurological function, or fertility and reproductive ability of first generation (F1) pups were noted, but postnatal body weights for F1 pups delivered to dams receiving 320 and 1280 mg/kg/day tazobactam were significantly reduced 21 days after delivery. The second generation (F2) fetuses were normal for all doses of tazobactam. No adverse effects on maternal reproduction were observed at doses up to 320 mg/kg/day and F1 body weights were not reduced at a dose of 40 mg/kg/day (respectively equivalent to approximately 1.0 and 0.1 times the MRHD of 1 gram every 8 hours based on body surface area comparison).

8.2 Lactation

Risk Summary

There are no data on the presence of ceftolozane or tazobactam in human milk. There are no data on the effects of tazobactam or ceftolozane on the breastfed infant, or the effects on milk production.

The developmental and health benefits of breastfeeding should be considered along with the mother's clinical need for ZERBAXA and any potential adverse effects on the breastfed child from ZERBAXA or from the underlying maternal conditions.

8.4 Pediatric Use

Complicated Intra-abdominal Infections (cIAI) and Complicated Urinary Tract Infections (cUTI), including Pyelonephritis

The safety and effectiveness of ZERBAXA for the treatment of cIAI and cUTI have been established in pediatric patients aged birth to less than 18 years old. Use of ZERBAXA in these age groups is supported by evidence from adequate and well-controlled studies of ZERBAXA in adults with cUTI and cIAI and additional pharmacokinetic and safety data from pediatric trials [see Clinical Pharmacology (12.3) and Clinical Studies (14.1 and 14.2)].

The safety profile of ZERBAXA in pediatric patients was similar to adults with cIAI and cUTI, treated with ZERBAXA [see Adverse Reactions (6.1)].

There is insufficient information to recommend dosage adjustment for pediatric patients younger than 18 years of age with cIAI and cUTI with eGFR 50 mL/min/1.73m^2 or less [see Dosage and Administration (2.4) and Clinical Pharmacology (12.3)].

ZERBAXA is not recommended in pediatric patients who have an eGFR 50 mL/min/1.73m^2 or less. Pediatric patients born at term or pre-term may not have an eGFR of 50 mL/min/1.73m^2 or greater at birth or within the first few months of life.

Hospital-acquired Bacterial Pneumonia and Ventilator-associated Bacterial Pneumonia (HABP/VABP)

The safety and effectiveness of ZERBAXA in pediatric patients have not been established for the treatment of HABP and VABP.

8.5 Geriatric Use

Of the 1015 patients treated with ZERBAXA in the Phase 3 cIAI and cUTI clinical trials, 250 (24.6%) were 65 years or older, including 113 (11.1%) 75 years or older. The incidence of adverse events in both treatment groups was higher in older subjects (65 years or older) in the trials for both indications. In the cIAI trial, cure rates in the elderly (aged 65 years and older) in the ZERBAXA plus metronidazole arm were 69/100 (69%) and in the comparator arm were 70/85 (82.4%). This finding in the elderly population was not observed in the cUTI trial.

Of the 361 patients treated with ZERBAXA in the Phase 3 HABP/VABP clinical trial, 160 (44.3%) were 65 years or older, including 83 (23%) 75 years or older. The incidence of adverse events in both treatment groups was higher in older subjects (65 years or older). In the trial, Day 28 all-cause mortality rates in the elderly (aged 65 years and older) were comparable between treatment arms:50/160 (31.3%) in the ZERBAXA arm and 54/160 (33.8%) in the comparator arm.

ZERBAXA is substantially excreted by the kidney and the risk of adverse reactions to ZERBAXA may be greater in patients with renal impairment. Because elderly patients are more likely to have decreased renal function, care should be taken in dose selection, and it may be useful to monitor renal function. Adjust dosage for elderly patients based on renal function [see Dosage and Administration (2.2) and Clinical Pharmacology (12.3)].

8.6 Patients with Renal Impairment

Adult Patients

Dosage adjustment is required in adult patients with CrCl 50 mL/min or less, including adult patients with ESRD on HD [see Dosage and Administration (2.2), Warnings and Precautions (5.1) and Clinical Pharmacology (12.3)].

Pediatric Patients

No dose adjustment has been established in pediatric patients aged birth to less than 18 years of age with eGFR 50 mL/min/1.73 m^2 or less [see Clinical Pharmacology (12.3)].

10 OVERDOSAGE

In the event of overdose, discontinue ZERBAXA and provide general supportive treatment. ZERBAXA can be removed by hemodialysis. Approximately 66% of ceftolozane, 56% of tazobactam, and 51% of the tazobactam metabolite M1 were removed by dialysis. No information is available on the use of hemodialysis to treat overdosage.

11 DESCRIPTION

ZERBAXA (ceftolozane and tazobactam) is an antibacterial combination product consisting of the cephalosporin antibacterial drug ceftolozane sulfate and the beta-lactamase inhibitor tazobactam sodium for intravenous administration.

Ceftolozane sulfate is a semi-synthetic antibacterial drug of the beta-lactam class for parenteral administration. The chemical name of ceftolozane sulfate is 1H-Pyrazolium, 5-amino-4-[[[(2-aminoethyl)amino]carbonyl]amino]-2-[[(6R,7R)-7-[[(2Z)-2-(5-amino-1,2,4-thiadiazol-3-yl)-2-[(1-carboxy-1-methylethoxy)imino]acetyl]amino]-2-carboxy-8-oxo-5-thia-1-azabicyclo[4.2.0]oct-2-en-3-yl]methyl]-1-methyl-,sulfate (1:1). The molecular formula is C23H31N12O8S2^+∙HSO4^- and the molecular weight is 764.77.

Figure 1: Chemical structure of ceftolozane sulfate

Tazobactam sodium, a derivative of the penicillin nucleus, is a penicillanic acid sulfone. Its chemical name is sodium (2S,3S,5R)-3-methyl-7-oxo-3-(1H-1,2,3-triazol-1-ylmethyl)-4-thia-1-azabicyclo[3.2.0]heptane-2-carboxylate-4,4-dioxide. The chemical formula is C10H11N4NaO5S and the molecular weight is 322.3.

Figure 2: Chemical structure of tazobactam sodium

ZERBAXA 1.5 g (ceftolozane and tazobactam) for injection is a white to yellow sterile powder for reconstitution consisting of ceftolozane 1 g (equivalent to 1.147 g of ceftolozane sulfate) and tazobactam 0.5 g (equivalent to 0.537 g of tazobactam sodium) per vial, packaged in single-dose glass vials. The product contains sodium chloride (487 mg/vial) as a stabilizing agent, citric acid (21 mg/vial), and L-arginine (approximately 600 mg/vial) as excipients.

12 CLINICAL PHARMACOLOGY

12.1 Mechanism of Action

ZERBAXA is an antibacterial drug [see Clinical Pharmacology (12.4)].

12.2 Pharmacodynamics

As with other beta-lactam antibacterial agents, the percent time of dosing interval that the plasma concentration of ceftolozane exceeds the minimum inhibitory concentration (MIC) of the infecting organism has been shown to be the best predictor of efficacy in animal models of infection. The percent time of dosing interval that the plasma concentration of tazobactam exceeds a threshold concentration has been determined to be the parameter that best predicts the efficacy of tazobactam in in vitro and in vivo models. The exposure-response analyses in efficacy and safety clinical trials for cIAI, cUTI, and HABP/VABP support the recommended dose regimens of ZERBAXA.

Cardiac Electrophysiology

In a randomized, positive and placebo-controlled crossover thorough QTc study, 51 healthy subjects were administered a single therapeutic dose of ZERBAXA 1.5 gram (ceftolozane 1 g and tazobactam 0.5 g) and a supratherapeutic dose of ZERBAXA 4.5 gram (ceftolozane 3 g and tazobactam 1.5 g). No significant effects of ZERBAXA on heart rate, electrocardiogram morphology, PR, QRS, or QT interval were detected.

12.3 Pharmacokinetics

Ceftolozane and tazobactam pharmacokinetics are similar following single- and multiple-dose administrations. The Cmax and AUC of ceftolozane and tazobactam increase in proportion to dose.

The mean steady-state population pharmacokinetic parameters of ZERBAXA in patients with cIAI and cUTI receiving 1-hour intravenous infusions of ZERBAXA 1.5 g (ceftolozane 1 g and tazobactam 0.5 g) or patients with HABP/VABP receiving 1-hour intravenous infusions of ZERBAXA 3 g (ceftolozane 2 g and tazobactam 1 g) every 8 hours are summarized in Table 9.

Table 9: Mean (SD) Steady-State Plasma Population Pharmacokinetic Parameters of ZERBAXA (ceftolozane and tazobactam) after Multiple Intravenous 1-hour Infusions of ZERBAXA 1.5 g (ceftolozane 1 g and tazobactam 0.5 g) or 3 g (ceftolozane 2 g and tazobactam 1 g) Every 8 Hours in Adult Patients with CrCl Greater than 50 mL/min
PK parameters | ZERBAXA 1.5 g (ceftolozane 1 g and tazobactam 0.5 g) in cIAI and cUTI Patients |  | ZERBAXA 3 g (ceftolozane 2 g and tazobactam 1 g) in HABP/VABP Patients
PK parameters | Ceftolozane (n=317) | Tazobactam (n=244) | Ceftolozane (n=247) | Tazobactam (n=247)
Cmax (mcg/mL) | 65.7 (27) | 17.8 (9) | 105 (46) | 26.4 (13)
AUC0-8,ss (mcg∙h/mL) | 186 (74) | 35.8 (57) | 392 (236) | 73.3 (76)

Distribution

The binding of ceftolozane and tazobactam to human plasma proteins is approximately 16% to 21% and 30%, respectively. The mean (CV%) steady-state volume of distribution of ZERBAXA in healthy adult males (n = 51) following a single intravenous dose of ZERBAXA 1.5 g (ceftolozane 1 g and tazobactam 0.5 g) was 13.5 L (21%) and 18.2 L (25%) for ceftolozane and tazobactam, respectively, similar to extracellular fluid volume.

Following 1-hour intravenous infusions of ZERBAXA 3 g (ceftolozane 2 g and tazobactam 1 g) or adjusted based on renal function every 8 hours in ventilated patients with confirmed or suspected pneumonia (N=22), mean pulmonary epithelial lining fluid-to-free plasma AUC ratios of ceftolozane and tazobactam were approximately 50% and 62%, respectively, and are similar to those in healthy subjects (approximately 61% and 63%, respectively) receiving ZERBAXA 1.5 g (ceftolozane 1 g and tazobactam 0.5 g). Minimum ceftolozane and tazobactam epithelial lung lining fluid concentrations in ventilated subjects at the end of the dosing interval were 8.2 mcg/mL and 1.0 mcg/mL, respectively.

Elimination

Ceftolozane is eliminated from the body by renal excretion with a mean half-life of approximately 3 to 4 hours. Tazobactam is eliminated by renal excretion and metabolism with a plasma mean half-life of approximately 2 to 3 hours. The elimination half-life (t1/2) of ceftolozane or tazobactam is independent of dose.

Metabolism

Ceftolozane does not appear to be metabolized to any appreciable extent and is not a substrate for CYP enzymes. The beta-lactam ring of tazobactam is hydrolyzed to form the pharmacologically inactive tazobactam metabolite M1.

Excretion

Ceftolozane, tazobactam and the tazobactam metabolite M1 are excreted by the kidneys. Following administration of a single ZERBAXA 1.5 g (ceftolozane 1 g and tazobactam 0.5 g) intravenous dose to healthy male adults, greater than 95% of ceftolozane was excreted in the urine as unchanged parent drug. More than 80% of tazobactam was excreted as the parent compound with the remainder excreted as the tazobactam M1 metabolite. After a single dose of ZERBAXA, renal clearance of ceftolozane (3.41 – 6.69 L/h) was similar to plasma CL (4.10 to 6.73 L/h) and similar to the glomerular filtration rate for the unbound fraction, suggesting that ceftolozane is eliminated by the kidney via glomerular filtration. Tazobactam is a substrate for OAT1 and OAT3 transporters and its elimination has been shown to be inhibited by probenecid, an inhibitor of OAT1/3.

Specific Populations

Dose adjustment is not warranted on the basis of age (18 years and older), gender, or race/ethnicity. No significant differences in the pharmacokinetics of ceftolozane and tazobactam were observed based on age (18 years and older), gender, weight, or race/ethnicity.

Patients with Renal Impairment

The ceftolozane dose normalized geometric mean AUC increased up to 1.26-fold, 2.5-fold, and 5-fold in subjects with CrCl 80-51 mL/min, 50-30 mL/min, and 29-15 mL/min, respectively, compared to healthy subjects with normal renal function. The respective tazobactam dose normalized geometric mean AUC increased approximately up to 1.3-fold, 2-fold, and 4-fold. To maintain similar systemic exposures to those with normal renal function, dosage adjustment is required [see Dosage and Administration (2.2)].

In subjects with ESRD on HD, approximately two-thirds of the administered ZERBAXA dose is removed by HD. A single loading dose of ZERBAXA followed by a maintenance dose administered every 8 hours for the remainder of the treatment period is recommended in patients with ESRD on HD. On HD days, administer the dose at the earliest possible time following completion of HD. [See Dosage and Administration (2.2).]

Patients with Augmented Renal Function

Following a single 1-hour intravenous infusion of ZERBAXA 3 g (ceftolozane 2 g and tazobactam 1 g) to critically-ill patients with CrCl greater than or equal to 180 mL/min (N=10), mean terminal half-life values of ceftolozane and tazobactam were 2.6 hours and 1.5 hours, respectively. No dose adjustment of ZERBAXA is recommended for HABP/VABP patients with augmented renal function [see Clinical Studies (14.3)].

Patients with Hepatic Impairment

As ZERBAXA does not undergo hepatic metabolism, the systemic clearance of ZERBAXA is not expected to be affected by hepatic impairment.

No dose adjustment is recommended for ZERBAXA in subjects with hepatic impairment.

Geriatric Patients

In a population pharmacokinetic analysis of ZERBAXA, no clinically relevant differences in exposure were observed with regard to age.

No dose adjustment of ZERBAXA based on age is recommended. Dosage adjustment for ZERBAXA in geriatric patients should be based on renal function [see Dosage and Administration (2.2)].

Pediatric Patients

The pharmacokinetics of ceftolozane and tazobactam in pediatric patients (birth to <18 years) were evaluated from 3 clinical studies: patients with proven or suspected gram-negative infection, cIAI, and cUTI. Ceftolozane exposures were numerically higher in pediatric patients with cUTI compared to pediatric patients with cIAI, however, such a difference was not observed for tazobactam (Table 10 and Table 11) [see Clinical Studies 14.2].

In patients with cIAI (Table 10) and cUTI (Table 11) total body clearance of both ceftolozane and tazobactam increases with age, with values in adolescents approaching those in the adult population. Whereas elimination half-life tends to decrease with a decrease of age. While ceftolozane exposures in pediatric patients with cIAI and cUTI overlap with the range of exposures seen in adults, in general they are lower than mean exposures in adults. Tazobactam exposures are comparable between pediatric and adult patients except for patients aged birth to <3 months (Group 5) with cUTI, who had higher exposures.

Population pharmacokinetic analyses and target attainment simulations in pediatric patients with cIAI and cUTI demonstrated that the recommended pediatric dosing regimens for patients from birth to less than 18 years with eGFR greater than 50 mL/min/1.73 m^2 result in no clinically relevant differences in systemic exposure to those in adult patients given ZERBAXA 1.5 grams.

There is insufficient information to assess the exposure of ZERBAXA in the pediatric patients with eGFR ≤ 50 mL/min/1.73 m^2.

Table 10: Steady-State Plasma Population Pharmacokinetic Parameters (Mean and SD) of ZERBAXA (ceftolozane and tazobactam) in Pediatric cIAI Patients [One patient was enrolled in Group 4 in the C/T arm but discontinued before the day of PK sample collection; one participant was enrolled for Group 5 in the C/T arm with steady-state ceftolozane PK parameter values: AUC0-8=173 mcg*h/mL; Ceoi=43.4 mcg/mL; and with tazobactam PK parameter values: AUC0-8=69.9 mcg*h/mL; Ceoi=30.5 mcg/mL.]
Patient Characteristics | Group 1 (12 to <18 years) | Group 2 (6 to <12 years) | Group 3 (2 to <6 years)
 | N=16 | N=30 | N=20
Ceftolozane
AUC0-8 (mcg•h/mL) | 123 (46) | 116 (30) | 98.8 (26)
Ceoi (mcg/mL) | 51.1 (21) | 53.7 (18) | 42.4 (13)
t1/2 (hr) | 2.2 (0.4) | 1.8 (0.2) | 1.7 (0.3)
Vss (L) | 23.0 (14.6) | 11.5 (5.7) | 7.4 (3.2)
Clearance (L/h) | 9.55 (4.70) | 5.81 (2.15) | 3.58 (1.12)
Tazobactam
AUC0-8 (mcg•h/mL) | 31.7 (16) | 30.1 (7) | 23.4 (6)
Ceoi (mcg/mL) | 21.7 (10) | 21.4 (6) | 16.9 (6)
t1/2 (hr) | 1.3 (0.2) | 1.1 (0.2) | 1.0 (0.2)
Vss (L) | 18.8 (10.7) | 10.6 (6.2) | 7.1 (4.0)
Clearance (L/h) | 18.87 (7.54) | 11.02 (4.06) | 7.62 (2.40)
AUC0-8, area under the curve in the dosing interval 0 to 8 hours at steady-state; Ceoi, concentration at the end of infusion; CL, elimination clearance; SD, standard deviation; t1/2, terminal half-life; Vss, steady-state volume of distribution.

Table 11: Steady-State Plasma Population Pharmacokinetic Parameters (Mean and SD) of ZERBAXA (ceftolozane and tazobactam) in Pediatric cUTI Patients
Patient Characteristics | Group 1 (12 to <18 years) | Group 2 (6 to <12 years) | Group 3 (2 to <6 years) | Group 4 (3 months to <2 years) | Group 5 (Birth to <3 months)
 | N=14 | N=19 | N=20 | N=22 | N=14
Ceftolozane
AUC0-8 (mcg•h/mL) | 177 (65) | 145 (54) | 133 (49) | 129 (57) | 144 (39)
Ceoi (mcg/mL) | 68.7 (21) | 60.8 (20) | 60.3 (24) | 50.3 (20) | 43.1 (12)
t1/2 (hr) | 2.3 (0.4) | 2.0 (0.6) | 1.8 (0.4) | 2.0 (0.7) | 2.7 (0.6)
Vss (L) | 15.8 (5.5) | 10.7 (5.2) | 5.4 (2.1) | 3.7 (2.5) | 2.5 (1.0)
Clearance (L/h) | 6.31 (2.17) | 4.84 (2.18) | 2.59 (0.69) | 1.53 (0.64) | 0.75 (0.34)
Tazobactam
AUC0-8 (mcg•h/mL) | 35.0 (12) | 26.7 (10) | 26.6 (8) | 28.6 (13) | 44.6 (15)
Ceoi (mcg/mL) | 22.9 (8) | 19.2 (7) | 19.9 (7) | 18.9 (8) | 25.9 (10)
t1/2 (hr) | 1.3 (0.5) | 1.2 (0.4) | 1.0 (0.3) | 1.1 (0.4) | 1.2 (0.7)
Vss (L) | 16.0 (6.6) | 10.6 (8.2) | 5.1 (2.7) | 3.7 (3.4) | 1.5 (0.8)
Clearance (L/h) | 15.67 (4.49) | 12.83 (5.39) | 6.37 (2.02) | 3.53 (1.71) | 1.32 (0.81)
AUC0-8, area under the curve in the dosing interval 0 to 8 hours at steady-state; Ceoi, concentration at the end of infusion; CL, elimination clearance; SD, standard deviation; t1/2, terminal half-life; VSS, steady-state volume of distribution.

For ZERBAXA dosage recommendation in pediatric cIAI and cUTI patients, refer to table 2 [see Dosage and Administration (2.1)].

Drug Interactions

No drug-drug interaction was observed between ceftolozane and tazobactam in a clinical study in 16 healthy subjects. In vitro and in vivo data indicate that ZERBAXA is unlikely to cause clinically relevant drug-drug interactions related to CYPs and transporters at therapeutic concentrations.

Drug Metabolizing Enzymes

In vivo data indicated that ZERBAXA is not a substrate for CYPs. Thus, clinically relevant drug-drug interactions involving inhibition or induction of CYPs by other drugs are unlikely to occur.

In vitro studies demonstrated that ceftolozane, tazobactam and the M1 metabolite of tazobactam did not inhibit CYP1A2, CYP2B6, CYP2C8, CYP2C9, CYP2C19, CYP2D6, or CYP3A4 and did not induce CYP1A2, CYP2B6, or CYP3A4 at therapeutic plasma concentrations. In vitro induction studies in primary human hepatocytes demonstrated that ceftolozane, tazobactam, and the tazobactam metabolite M1 decreased CYP1A2 and CYP2B6 enzyme activity and mRNA levels in primary human hepatocytes as well as CYP3A4 mRNA levels at supratherapeutic plasma concentrations. Tazobactam metabolite M1 also decreased CYP3A4 activity at supratherapeutic plasma concentrations. A clinical drug-drug interaction study was conducted and results indicated drug interactions involving CYP1A2 and CYP3A4 inhibition by ZERBAXA are not anticipated.

Membrane Transporters

Ceftolozane and tazobactam were not substrates for P-gp or BCRP, and tazobactam was not a substrate for OCT2, in vitro at therapeutic concentrations.

Tazobactam is a known substrate for OAT1 and OAT3. Co-administration of tazobactam with the OAT1/OAT3 inhibitor probenecid has been shown to prolong the half-life of tazobactam by 71%. Co-administration of ZERBAXA with drugs that inhibit OAT1 and/or OAT3 may increase tazobactam plasma concentrations.

In vitro data indicate that ceftolozane did not inhibit P-gp, BCRP, OATP1B1, OATP1B3, OCT1, OCT2, MRP, BSEP, OAT1, OAT3, MATE1, or MATE2-K in vitro at therapeutic plasma concentrations.

In vitro data indicate that neither tazobactam nor the tazobactam metabolite M1 inhibit P-gp, BCRP, OATP1B1, OATP1B3, OCT1, OCT2, or BSEP transporters at therapeutic plasma concentrations. In vitro, tazobactam inhibited human OAT1 and OAT3 transporters with IC50 values of 118 and 147 mcg/mL, respectively. A clinical drug-drug interaction study was conducted and results indicated clinically relevant drug interactions involving OAT1/OAT3 inhibition by ZERBAXA are not anticipated.

12.4 Microbiology

Mechanism of Action

Ceftolozane belongs to the cephalosporin class of antibacterial drugs. The bactericidal action of ceftolozane results from inhibition of cell wall biosynthesis, and is mediated through binding to penicillin-binding proteins (PBPs). Ceftolozane is an inhibitor of PBPs of P. aeruginosa (e.g., PBP1b, PBP1c, and PBP3) and E. coli (e.g., PBP3).

Tazobactam sodium has little clinically relevant in vitro activity against bacteria due to its reduced affinity to penicillin-binding proteins. It is an irreversible inhibitor of some beta-lactamases (e.g., certain penicillinases and cephalosporinases), and can bind covalently to some chromosomal and plasmid-mediated bacterial beta-lactamases.

Resistance

Mechanisms of beta-lactam resistance may include the production of beta-lactamases, modification of PBPs by gene acquisition or target alteration, up-regulation of efflux pumps, and loss of outer membrane porin.

Clinical isolates may produce multiple beta-lactamases, express varying levels of beta-lactamases, or have amino acid sequence variations, and other resistance mechanisms that have not been identified.

Culture and susceptibility information and local epidemiology should be considered in selecting or modifying antibacterial therapy.

ZERBAXA demonstrated in vitro activity against Enterobacteriaceae in the presence of some extended-spectrum beta-lactamases (ESBLs) and other beta-lactamases of the following groups: TEM, SHV, CTX-M, and OXA. ZERBAXA is not active against bacteria that produce serine carbapenemases [K. pneumoniae carbapenemase (KPC)], and metallo-beta-lactamases.

In ZERBAXA clinical trials, some isolates of Enterobacteriaceae with minimum inhibitory concentration to ZERBAXA of ≤2 mcg/mL produced beta-lactamases. These isolates produced one or more beta-lactamases of the following enzyme groups: CTX-M, OXA, TEM, or SHV.

Some of these beta-lactamases were also produced by isolates of Enterobacteriaceae with minimum inhibitory concentration to ZERBAXA >2 mcg/mL.

ZERBAXA demonstrated in vitro activity against P. aeruginosa isolates tested that had chromosomal AmpC, loss of outer membrane porin (OprD), or up regulation of efflux pumps (MexXY, MexAB).

Isolates resistant to other cephalosporins may be susceptible to ZERBAXA, although cross-resistance may occur.

Interaction with Other Antimicrobials

In vitro synergy studies suggest no antagonism between ZERBAXA and other antibacterial drugs (e.g., meropenem, amikacin, aztreonam, levofloxacin, tigecycline, rifampin, linezolid, daptomycin, vancomycin, and metronidazole).

Antimicrobial Activity

ZERBAXA has been shown to be active against the following bacteria, both in vitro and in clinical infections [see Indications and Usage (1)].

Complicated Intra-abdominal Infections

Gram-negative bacteria:

Enterobacter cloacae
  Escherichia coli
  Klebsiella oxytoca
  Klebsiella pneumoniae
  Proteus mirabilis
  Pseudomonas aeruginosa

Gram-positive bacteria:

Streptococcus anginosus
  Streptococcus constellatus
  Streptococcus salivarius

Anaerobic bacteria:

Bacteroides fragilis

Complicated Urinary Tract Infections, Including Pyelonephritis

Gram-negative bacteria:

Escherichia coli
  Klebsiella pneumoniae
  Proteus mirabilis
  Pseudomonas aeruginosa

Hospital-acquired Bacterial Pneumonia and Ventilator-associated Bacterial Pneumonia (HABP/VABP)

Gram-negative bacteria:

Enterobacter cloacae
  Escherichia coli
  Haemophilus influenzae
  Klebsiella oxytoca
  Klebsiella pneumoniae
  Proteus mirabilis
  Pseudomonas aeruginosa
  Serratia marcescens

The following in vitro data are available, but their clinical significance is unknown. At least 90 percent of the following bacteria exhibit an in vitro minimum inhibitory concentration (MIC) less than or equal to the susceptible breakpoint for ceftolozane and tazobactam against isolates of similar genus or organism group. However, the efficacy of ZERBAXA in treating clinical infections due to these bacteria has not been established in adequate and well-controlled clinical trials.

Gram-negative bacteria:

Citrobacter koseri
  Klebsiella aerogenes
  Morganella morganii
  Proteus vulgaris
  Providencia rettgeri
  Providencia stuartii
  Serratia liquefaciens

Gram-positive bacteria:

Streptococcus agalactiae
  Streptococcus intermedius

Susceptibility Testing

For specific information regarding susceptibility test interpretive criteria and associated test methods and quality control standards recognized by FDA for ceftolozane and tazobactam, please see:
https://www.fda.gov/STIC .

13 NONCLINICAL TOXICOLOGY

13.1 Carcinogenesis, Mutagenesis, Impairment of Fertility

Long-term carcinogenicity studies in animals have not been conducted with ZERBAXA, ceftolozane, or tazobactam.

ZERBAXA was negative for genotoxicity in an in vitro mouse lymphoma assay and an in vivo rat bone-marrow micronucleus assay. In an in vitro chromosomal aberration assay in Chinese hamster ovary cells, ZERBAXA was positive for structural aberrations.

Ceftolozane was negative for genotoxicity in an in vitro microbial mutagenicity (Ames) assay, an in vitro chromosomal aberration assay in Chinese hamster lung fibroblast cells, an in vitro mouse lymphoma assay, an in vitro HPRT assay in Chinese hamster ovary cells, an in vivo mouse micronucleus assay, and an in vivo unscheduled DNA synthesis (UDS) assay.

Tazobactam was negative for genotoxicity in an in vitro microbial mutagenicity (Ames) assay, an in vitro chromosomal aberration assay in Chinese hamster lung cells, an in vitro mammalian point-mutation (Chinese hamster ovary cell HPRT) assay, an in vivo mouse bone-marrow micronucleus assay, and an in vivo UDS assay.

Ceftolozane was administered in a fertility study at intravenous doses of 100, 300, and 1000 mg/kg/day to male rats for 28 days before mating and through the mating period and to female rats for 14 days before mating, through the mating period, and until the 7th day of gestation. Ceftolozane had no adverse effect on fertility in male or female rats at doses up to 1000 mg/kg/day (approximately 1.4 times the maximum recommended human dose (MRHD) of 2 grams every 8 hours based on AUC comparison).

In a rat fertility study, intraperitoneal tazobactam doses of 40, 160, and 640 mg/kg/day were administered twice-daily to male rats beginning 70 days before mating and through the mating period, and to female rats beginning 14 days before mating, during the mating period, and until Gestation Day 21. Male and female fertility parameters were not affected at doses less than or equal to 640 mg/kg/day (approximately 2 times the MRHD of 1 gram every 8 hours based on body surface comparison).

14 CLINICAL STUDIES

14.1 Complicated Intra-abdominal Infections

Adult Patients

A total of 979 adults hospitalized with cIAI were randomized and received study medications in a multinational, double-blind study comparing ZERBAXA 1.5 g (ceftolozane 1 g and tazobactam 0.5 g) intravenously every 8 hours plus metronidazole (500 mg intravenously every 8 hours) to meropenem (1 g intravenously every 8 hours) for 4 to 14 days of therapy. Complicated intra-abdominal infections included appendicitis, cholecystitis, diverticulitis, gastric/duodenal perforation, perforation of the intestine, and other causes of intra-abdominal abscesses and peritonitis. The majority of patients (75%) were from Eastern Europe; 6.3% were from the United States.

The primary efficacy endpoint was clinical response, defined as complete resolution or significant improvement in signs and symptoms of the index infection at the test-of-cure (TOC) visit which occurred 24 to 32 days after the first dose of study drug. The primary efficacy analysis population was the microbiological intent-to-treat (MITT) population, which included all patients who had at least 1 baseline intra-abdominal pathogen regardless of the susceptibility to study drug. The key secondary efficacy endpoint was clinical response at the TOC visit in the microbiologically evaluable (ME) population, which included all protocol-adherent MITT patients.

The MITT population consisted of 806 patients; the median age was 52 years and 57.8% were male. The most common diagnosis was appendiceal perforation or peri-appendiceal abscess, occurring in 47% of patients. Diffuse peritonitis at baseline was present in 34.2% of patients.

ZERBAXA plus metronidazole was non-inferior to meropenem with regard to clinical cure rates at the TOC visit in the MITT population. Clinical cure rates at the TOC visit are displayed by patient population in Table 12. Clinical cure rates at the TOC visit by pathogen in the MITT population are presented in Table 13.

Table 12: Clinical Cure Rates in a Phase 3 Trial of Complicated Intra-Abdominal Infections
Analysis Population | ZERBAXA plus Metronidazole [ZERBAXA 1.5 g intravenously every 8 hours + metronidazole 500 mg intravenously every 8 hours] n/N (%) | Meropenem [1 gram intravenously every 8 hours] n/N (%) | Treatment Difference (95% CI) [The 95% confidence interval (CI) was calculated as an unstratified Wilson Score CI.]
MITT | 323/389 (83) | 364/417 (87.3) | -4.3 (-9.2, 0.7)
ME | 259/275 (94.2) | 304/321 (94.7) | -0.5 (-4.5, 3.2)

Table 13: Clinical Cure Rates by Pathogen in a Phase 3 Trial of Complicated Intra-abdominal Infections (MITT Population)
Organism Group Pathogen | ZERBAXA plus Metronidazole n/N (%) | Meropenem n/N (%)
Aerobic Gram-negative
Escherichia coli | 216/255 (84.7) | 238/270 (88.1)
Klebsiella pneumoniae | 31/41 (75.6) | 27/35 (77.1)
Pseudomonas aeruginosa | 30/38 (79) | 30/34 (88.2)
Enterobacter cloacae | 21/26 (80.8) | 24/25 (96)
Klebsiella oxytoca | 14/16 (87.5) | 24/25 (96)
Proteus mirabilis | 11/12 (91.7) | 9/10 (90)
Aerobic Gram-positive
Streptococcus anginosus | 26/36 (72.2) | 24/27 (88.9)
Streptococcus constellatus | 18/24 (75) | 20/25 (80)
Streptococcus salivarius | 9/11 (81.8) | 9/11 (81.8)
Anaerobic Gram-negative
Bacteroides fragilis | 42/47 (89.4) | 59/64 (92.2)
Bacteroides ovatus | 38/45 (84.4) | 44/46 (95.7)
Bacteroides thetaiotaomicron | 21/25 (84) | 40/46 (87)
Bacteroides vulgatus | 12/15 (80) | 24/26 (92.3)

In a subset of the E. coli and K. pneumoniae isolates from both arms of the cIAI Phase 3 trial that met pre-specified criteria for beta-lactam susceptibility, genotypic testing identified certain ESBL groups (e.g., TEM, SHV, CTX-M, OXA) in 53/601 (9%). Cure rates in this subset were similar to the overall trial results. In vitro susceptibility testing showed that some of these isolates were susceptible to ZERBAXA (MIC ≤2 mcg/mL), while some others were not susceptible (MIC >2 mcg/mL). Isolates of a specific genotype were seen in patients who were deemed to be either successes or failures.

Pediatric Patients

The pediatric cIAI trial was a randomized, double-blind, multi-center, active controlled trial conducted in hospitalized patients from birth to less than 18 years (NCT03217136). Patients were randomized in a 3:1 ratio to either intravenous (IV) ZERBAXA [see Dosage and Administration (2.2)] plus metronidazole (10 mg/kg IV every 8 hours), or meropenem (20 mg/kg IV every 8 hours) plus placebo. Patients received IV study treatment for a minimum of 3 days before an optional switch to oral step-down therapy at the discretion of the investigator to complete a total of 5 to 14 days of antibacterial therapy.

The modified intent-to-treat (MITT) population consisted of 91 patients (N=70 in the ZERBAXA plus metronidazole group; N=21 in the meropenem plus placebo group) who were randomized and received at least one dose of study treatment. The median age of patients was 8.2 years and 8.5 years in the ZERBAXA plus metronidazole and meropenem plus placebo groups, respectively. In the ZERBAXA plus metronidazole group, enrollment by age group was as follows: 12 to <18 y: n=16, 6 to <12 y: n=30, 2 to <6 y: n=22, 3 months to <2 y: n=1, birth to <3 months: n=1. Patients treated with ZERBAXA plus metronidazole were predominantly male (67%) and White (87%). Patients treated with meropenem plus placebo were predominantly female (71%) and White (91%). Most patients in the MITT population had a diagnosis of complicated appendicitis at baseline (ZERBAXA plus metronidazole: 91.4%; meropenem plus placebo: 100%). The median (range) duration of IV study treatment was comparable between patients in the ZERBAXA plus metronidazole (6.3 [0.3 to 14.0] days) and meropenem plus placebo (6.0 [2.3 to 8.8] days) groups.

The primary objective of the study was to evaluate the safety and tolerability of ZERBAXA. Efficacy assessments were not powered for formal hypothesis testing of between-treatment group comparisons. At the TOC visit, which occurred 7 to 14 days after the last dose of study drug, a favorable clinical response was defined as complete resolution or marked improvement in signs and symptoms of the cIAI or return to pre-infection signs and symptoms such that no further antibiotic therapy (IV or oral) or surgical or drainage procedure was required for treatment of the cIAI. A summary of clinical response rates in the MITT and clinically evaluable (CE) populations at the TOC visit are presented in Table 14. The CE included all protocol adherent MITT patients with a clinical outcome at the visit of interest.

Table 14: Clinical Response Rates in a Pediatric Study of Complicated Intra-Abdominal Infections
Analysis Population | ZERBAXA plus metronidazole n/N (%) | Meropenem n/N (%) | Treatment Difference (95% CI) [The Miettinen & Nurminen method stratified by age group with Cochran-Mantel-Haenszel weights was used.]
MITT Population | 56/70 (80.0) | 21/21 (100.0) | -19.1 (-30.2, -2.9)
CE Population | 52/58 (89.7) | 19/19 (100.0) | -10.7 (-21.5, 6.8)

14.2 Complicated Urinary Tract Infections, Including Pyelonephritis

Adult Patients

A total of 1068 adults hospitalized with cUTI (including pyelonephritis) were randomized and received study medications in a multinational, double-blind study comparing ZERBAXA 1.5 g (ceftolozane 1 g and tazobactam 0.5 g) intravenously every 8 hours to levofloxacin (750 mg intravenously once daily) for 7 days of therapy. The primary efficacy endpoint was defined as complete resolution or marked improvement of the clinical symptoms and microbiological eradication (all uropathogens found at baseline at ≥10^5 were reduced to <10^4 CFU/mL) at the test-of-cure (TOC) visit 7 (± 2) days after the last dose of study drug. The primary efficacy analysis population was the microbiologically modified intent-to-treat (mMITT) population, which included all patients who received study medication and had at least 1 baseline uropathogen. The key secondary efficacy endpoint was the composite microbiological and clinical cure response at the TOC visit in the microbiologically evaluable (ME) population, which included protocol-adherent mMITT patients with a urine culture at the TOC visit.

The mMITT population consisted of 800 patients with cUTI, including 656 (82%) with pyelonephritis. The median age was 50.5 years and 74% were female. Concomitant bacteremia was identified in 62 (7.8%) patients at baseline; 608 (76%) patients were enrolled in Eastern Europe and 14 (1.8%) patients were enrolled in the United States.

ZERBAXA demonstrated efficacy with regard to the composite endpoint of microbiological and clinical cure at the TOC visit in both the mMITT and ME populations (Table 15). Composite microbiological and clinical cure rates at the TOC visit by pathogen in the mMITT population are presented in Table 16.

In the mMITT population, the composite cure rate in ZERBAXA-treated patients with concurrent bacteremia at baseline was 23/29 (79.3%).

Although a statistically significant difference was observed in the ZERBAXA arm compared to the levofloxacin arm with respect to the primary endpoint, it was likely attributable to the 212/800 (26.5%) patients with baseline organisms non-susceptible to levofloxacin. Among patients infected with a levofloxacin-susceptible organism at baseline, the response rates were similar (Table 15).

Table 15: Composite Microbiological and Clinical Cure Rates in a Phase 3 Trial of Complicated Urinary Tract Infections
Analysis Population | ZERBAXA [ZERBAXA 1.5 g intravenously every 8 hours] n/N (%) | Levofloxacin [750 mg intravenously once daily] n/N (%) | Treatment Difference (95% CI) [The 95% confidence interval was based on the stratified Newcombe method.]
mMITT | 306/398 (76.9) | 275/402 (68.4) | 8.5 (2.3, 14.6)
Levofloxacin resistant baseline pathogen(s) | 60/100 (60) | 44/112 (39.3)
No levofloxacin resistant baseline pathogen(s) | 246/298 (82.6) | 231/290 (79.7)
ME | 284/341 (83.3) | 266/353 (75.4) | 8.0 (2.0, 14.0)

Table 16: Composite Microbiological and Clinical Cure Rates in a Phase 3 Trial of Complicated Urinary Tract Infections, in Subgroups Defined by Baseline Pathogen (mMITT Population)
Pathogen | ZERBAXA n/N (%) | Levofloxacin n/N (%)
Escherichia coli | 247/305 (81) | 228/324 (70.4)
Klebsiella pneumoniae | 22/33 (66.7) | 12/25 (48)
Proteus mirabilis | 11/12 (91.7) | 6/12 (50)
Pseudomonas aeruginosa | 6/8 (75) | 7/15 (46.7)

In a subset of the E. coli and K. pneumoniae isolates from both arms of the cUTI Phase 3 trial that met pre-specified criteria for beta-lactam susceptibility, genotypic testing identified certain ESBL groups (e.g., TEM, SHV, CTX-M, OXA) in 104/687 (15%). Cure rates in this subset were similar to the overall trial results. In vitro susceptibility testing showed that some of these isolates were susceptible to ZERBAXA (MIC ≤2 mcg/mL), while some others were not susceptible (MIC >2 mcg/mL). Isolates of a specific genotype were seen in patients who were deemed to be either successes or failures.

Pediatric Patients

The cUTI pediatric trial was a randomized, double-blind multi-center, active controlled trial conducted in hospitalized patients from birth to less than 18 years (NCT03230838). Eligible patients were randomized in a 3:1 ratio to IV ZERBAXA or meropenem, respectively. Patients received IV study treatment for a minimum of 3 days before an optional switch to oral step-down therapy at the discretion of the investigator to complete a total of 7 to 14 days of antibacterial therapy.

The microbiologic modified intent-to-treat (mMITT) population consisted of 95 patients (N=71 in the ZERBAXA group; N=24 in the meropenem group) who were randomized and received at least one dose of study treatment and had an eligible uropathogen isolated from a baseline urine culture.

The median age of patients was 2.7 years and 1.6 years in the ZERBAXA and meropenem groups, respectively. In the ZERBAXA group, enrollment by age group was as follows: 12 to <18 y: n=10, 6 to <12 y: n=13, 2 to <6 y: n=14, 3 months to <2 y: n=20, birth to <3 months: n=14. Patients treated with ZERBAXA were predominantly female (56%) and White (99%). Patients treated with meropenem were predominantly female (63%) and White (100%). Most patients in the mMITT population had a diagnosis of pyelonephritis (ZERBAXA: 84.5%; meropenem: 79.2%). The most common baseline qualifying gram-negative uropathogens were Escherichia coli (ZERBAXA: 74.6%; meropenem: 87.5%), Klebsiella pneumoniae (8.5%; 4.2%), and Pseudomonas aeruginosa (7.0%; 8.3%).

The primary objective of the study was to evaluate the safety and tolerability of ZERBAXA. Efficacy assessments were not powered for formal hypothesis testing of between treatment group comparisons. At the TOC visit, which occurred 7 to 14 days after the last dose of study drug, a favorable clinical response was defined as complete resolution or marked improvement in signs and symptoms of the cUTI or return to pre-infection signs and symptoms, such that no further antibiotic therapy (IV or oral) was required for the treatment of the cUTI. A favorable microbiological response at the TOC was defined as eradication (all uropathogens found at baseline at ≥10^5 were reduced to <10^4 CFU/mL) of baseline uropathogens from the urine culture. A summary of clinical and microbiologic response rates in the mMITT population at the TOC visit is presented in Table 17.

Table 17: Clinical and Microbiological Response Rates in a Pediatric Study of Complicated Urinary Tract Infections
mMITT Population | ZERBAXA n/N (%) | Meropenem n/N (%) | Treatment Difference (95% CI) [The Miettinen & Nurminen method stratified by age group with Cochran-Mantel-Haenszel weights was used.]
Clinical Response Rate | 63/71 (88.7) | 23/24 (95.8) | -7.3 (-18.0, 10.1)
Microbiologic Response Rate | 60/71 (84.5) | 21/24 (87.5) | -3.0 (-17.1, 17.4)

14.3 Hospital-acquired Bacterial Pneumonia and Ventilator-associated Bacterial Pneumonia (HABP/VABP)

Adult Patients

A total of 726 adult patients hospitalized with HABP/VABP were enrolled in a multinational, double-blind study (NCT02070757) comparing ZERBAXA 3 g (ceftolozane 2 g and tazobactam 1 g) intravenously every 8 hours to meropenem (1 g intravenously every 8 hours) for 8 to 14 days of therapy. All patients had to be intubated and on mechanical ventilation at randomization.

Efficacy was assessed based on all-cause mortality at Day 28 and clinical cure, defined as complete resolution or significant improvement in signs and symptoms of the index infection at the test-of-cure (TOC) visit which occurred 7 to 14 days after the end of treatment. The analysis population was the intent-to-treat (ITT) population, which included all randomized patients.

Following a diagnosis of HABP/VABP and prior to receipt of first dose of study drug, if required, patients could have received up to a maximum of 24 hours of active non-study antibacterial drug therapy in the 72 hours preceding the first dose of study drug. Patients who had failed prior antibacterial drug therapy for the current episode of HABP/VABP could be enrolled if the baseline lower respiratory tract (LRT) culture showed growth of a Gram-negative pathogen while the patient was on the antibacterial therapy and all other eligibility criteria were met. Empiric therapy at baseline with linezolid or other approved therapy for Gram-positive coverage was required in all patients pending baseline LRT culture results. Adjunctive Gram-negative therapy was optional and allowed for a maximum of 72 hours in centers with a prevalence of meropenem-resistant P. aeruginosa more than 15%.

Of the 726 patients in the ITT population, the median age was 62 years and 44% of the population was 65 years of age and older, with 22% of the population 75 years of age and older. The majority of patients were White (83%), male (71%) and were from Eastern Europe (64%). The median APACHE II score was 17 and 33% of subjects had a baseline APACHE II score of greater than or equal to 20. All subjects were on mechanical ventilation and 519 (71%) had VABP. At randomization, 92% of subjects were in the ICU, 77% had been hospitalized for 5 days or longer, and 49% were ventilated for 5 days or longer. A total of 258 of 726 (36%) patients had CrCl less than 80 mL/min at baseline; among these, 99 (14%) had CrCl less than 50 mL/min. Patients with end-stage renal disease (CrCl less than 15 mL/min) were excluded from the trial. Approximately 13% of subjects were failing their current antibacterial drug therapy for HABP/VABP, and bacteremia was present at baseline in 15% of patients. Key comorbidities included diabetes mellitus, congestive heart failure, and chronic obstructive pulmonary disease at rates of 22%, 16%, and 12%, respectively. In both treatment groups, most subjects (63.1%) received between 8 and 14 days of study therapy as specified in the protocol.

Table 18 presents the results for Day 28 all-cause mortality and clinical cure at the TOC visit overall and by ventilated HABP and VABP.

Table 18: Day 28 All-cause Mortality and Clinical Cure Rates at TOC from a Phase 3 Study of Hospital-acquired Bacterial Pneumonia and Ventilator-associated Bacterial Pneumonia (HABP/VABP) (ITT Population)
Endpoint | ZERBAXA n/N (%) | Meropenem n/N (%) | Treatment Difference (95% CI) [The CI for overall treatment difference was based on the stratified Newcombe method with minimum risk weights. The CI for treatment difference of each primary diagnosis was based on the unstratified Newcombe method.]
Day 28 All-cause Mortality | 87/362 (24.0) | 92/364 (25.3) | 1.1 (-5.13, 7.39)
VABP | 63/263 (24.0) | 52/256 (20.3) | -3.6 (-10.74, 3.52)
Ventilated HABP | 24/99 (24.2) | 40/108 (37.0) | 12.8 (0.18, 24.75)
Clinical Cure at TOC Visit | 197/362 (54.4) | 194/364 (53.3) | 1.1 (-6.17, 8.29)
VABP | 147/263 (55.9) | 146/256 (57.0) | -1.1 (-9.59, 7.35)
Ventilated HABP | 50/99 (50.5) | 48/108 (44.4) | 6.1 (-7.44, 19.27)

In the ITT population, Day 28 all-cause mortality and clinical cure rates in patients with CrCl greater than or equal to 150 mL/min were similar between ZERBAXA and meropenem. In patients with bacteremia at baseline, Day 28 all-cause mortality rates were 23/64 (35.9%) for ZERBAXA-treated patients and 13/41 (31.7%) for meropenem-treated patients; clinical cure rates were 30/64 (46.9%) and 15/41 (36.6%), respectively.

Per pathogen Day 28 all-cause mortality and clinical cure at TOC were assessed in the microbiologic intention to treat population (mITT), which consisted of all randomized subjects who had a baseline lower respiratory tract (LRT) pathogen that was susceptible to both study treatments. In the mITT population, Klebsiella pneumoniae (113/425, 26.6%) and Pseudomonas aeruginosa (103/425, 24.2%) were the most prevalent pathogens isolated from baseline LRT cultures.

Day 28 all-cause mortality and clinical cure rates at TOC by pathogen in the mITT population are presented in Table 19. In the mITT population, clinical cure rates in patients with a Gram-negative pathogen at baseline were 139/215 (64.7%) for ZERBAXA and 115/204 (56.4%) for meropenem, respectively.

Table 19: Day 28 All-cause Mortality and Clinical Cure Rates at TOC by Baseline Pathogen from a Phase 3 Study of Hospital-acquired Bacterial Pneumonia and Ventilator-associated Bacterial Pneumonia (HABP/VABP) (mITT population)
Baseline Pathogen Category | Day 28 All-cause Mortality |  | Clinical Cure at TOC
Baseline Pathogen | ZERBAXA n/N (%) | Meropenem n/N (%) | ZERBAXA n/N (%) | Meropenem n/N (%)
Pseudomonas aeruginosa | 12/47 (25.5) | 10/56 (17.9) | 29/47 (61.7) | 34/56 (60.7)
Enterobacteriaceae | 27/161 (16.8) | 42/157 (26.8) | 103/161 (64.0) | 87/157 (55.4)
Enterobacter cloacae | 2/15 (13.3) | 8/14 (57.1) | 8/15 (53.3) | 4/14 (28.6)
Escherichia coli | 10/50 (20.0) | 11/42 (26.2) | 32/50 (64.0) | 26/42 (61.9)
Klebsiella oxytoca | 3/14 (21.4) | 3/12 (25.0) | 9/14 (64.3) | 7/12 (58.3)
Klebsiella pneumoniae | 7/51 (13.7) | 13/62 (21.0) | 34/51 (66.7) | 39/62 (62.9)
Proteus mirabilis | 5/22 (22.7) | 5/18 (27.8) | 13/22 (59.1) | 11/18 (61.1)
Serratia marcescens | 3/14 (21.4) | 1/12 (8.3) | 8/14 (57.1) | 7/12 (58.3)
Haemophilus influenzae | 0/20 (0) | 2/15 (13.3) | 17/20 (85.0) | 8/15 (53.3)

In a subset of Enterobacteriaceae isolates from both arms of the trial that met pre-specified criteria for beta-lactam susceptibility, genotypic testing identified certain ESBL groups (e.g., TEM, SHV, CTX-M, OXA) in 101/425 (23.8%). Day 28 all-cause mortality and clinical cure rates in this subset were similar to the overall trial results.

16 HOW SUPPLIED/STORAGE AND HANDLING

16.1 How Supplied

ZERBAXA 1.5 g (ceftolozane and tazobactam) for injection is supplied in single-dose vials containing ceftolozane 1 g (equivalent to 1.147 g of ceftolozane sulfate) and tazobactam 0.5 g (equivalent to 0.537 g of tazobactam sodium) per vial. Vials are supplied in cartons containing 10 vials.

(NDC 67919-030-01)

16.2 Storage and Handling

ZERBAXA vials should be stored refrigerated at 2 to 8°C (36 to 46°F) and protected from light.

The reconstituted solution, once diluted, may be stored for 24 hours at room temperature or for 7 days under refrigeration at 2 to 8° C (36 to 46°F). Discard unused portion.

17 PATIENT COUNSELING INFORMATION

Serious Allergic Reactions

Advise patient that allergic reactions, including serious allergic reactions, could occur and that serious reactions require immediate treatment. Ask patient about any previous hypersensitivity reactions to ZERBAXA, other beta-lactams (including cephalosporins) or other allergens [see Warnings and Precautions (5.2)].

Potentially Serious Diarrhea

Advise patient that diarrhea is a common problem caused by antibacterial drugs. Sometimes, frequent watery or bloody diarrhea may occur and may be a sign of a more serious intestinal infection. If severe watery or bloody diarrhea develops, tell patient to contact his or her healthcare provider [see Warnings and Precautions (5.3)].

Antibacterial Resistance

Patients should be counseled that antibacterial drugs including ZERBAXA should only be used to treat bacterial infections. They do not treat viral infections (e.g., the common cold). When ZERBAXA is prescribed to treat a bacterial infection, patients should be told that although it is common to feel better early in the course of therapy, the medication should be taken exactly as directed. Skipping doses or not completing the full course of therapy may (1) decrease the effectiveness of the immediate treatment and (2) increase the likelihood that bacteria will develop resistance and will not be treatable by ZERBAXA or other antibacterial drugs in the future [see Warnings and Precautions (5.4)].

Manufactured for: Merck Sharp & Dohme LLC
Rahway, NJ 07065, USA

Manufactured by: Steri-Pharma, LLC
Syracuse, NY 13202, USA

For patent information: www.msd.com/research/patent

Copyright © 2015-2022 Merck & Co., Inc., Rahway, NJ, USA, and its affiliates.
All rights reserved.

uspi-mk7625a-iv-2205r008

PRINCIPAL DISPLAY PANEL - 1.5 g Vial Carton

NDC 67919-030-01
10 Single-Dose vials

Zerbaxa®
1.5 g per vial*
(ceftolozane and tazobactam) for injection

*Ceftolozane 1 gram (equivalent to 1.147 g ceftolozane sulfate)
and Tazobactam 0.5 g (equivalent to 0.537 g tazobactam sodium)

For Intravenous Infusion

Rx only
Sterile